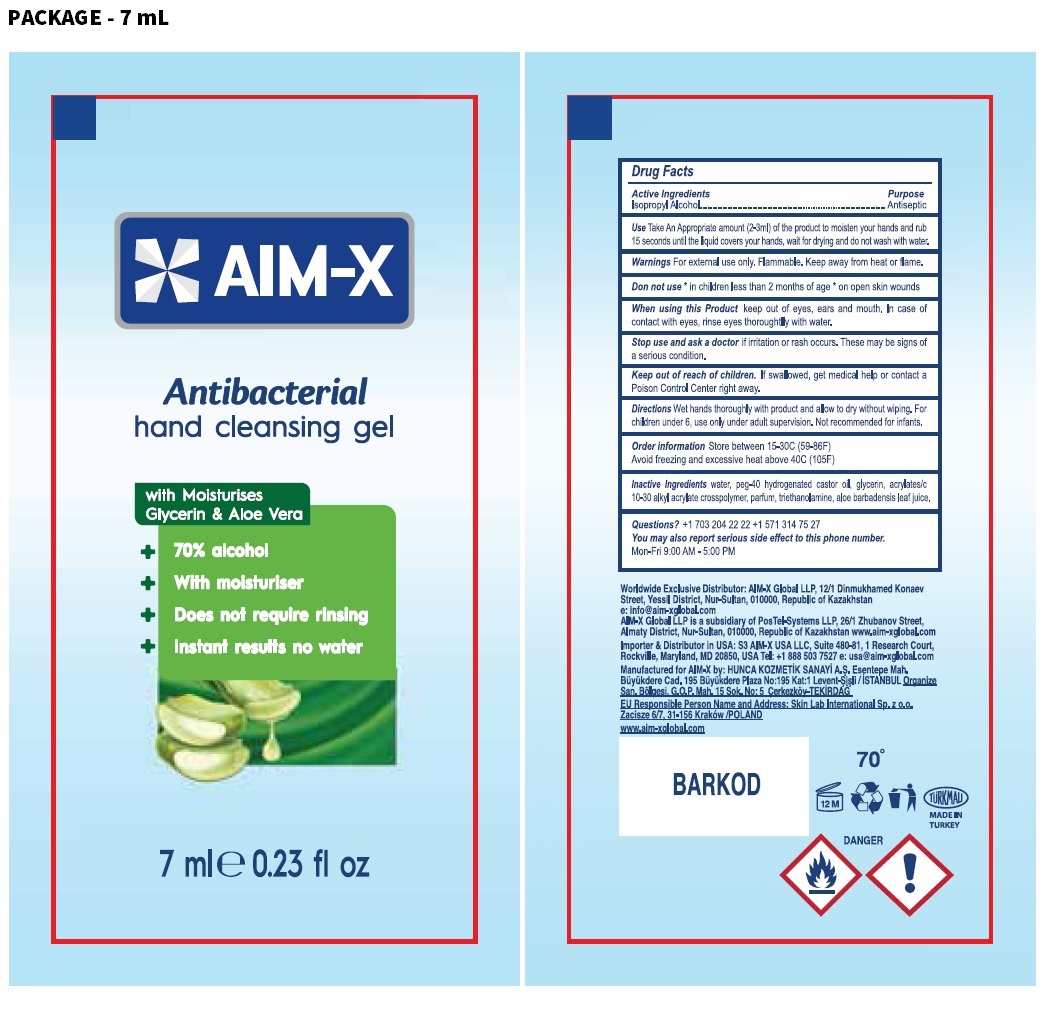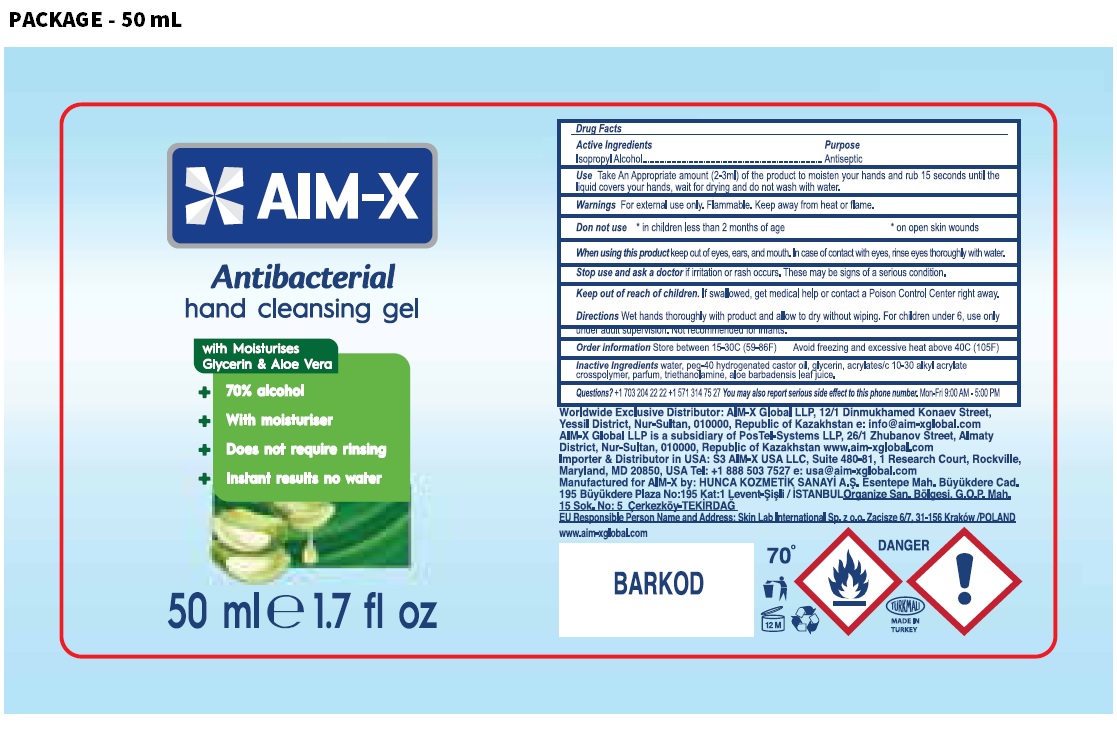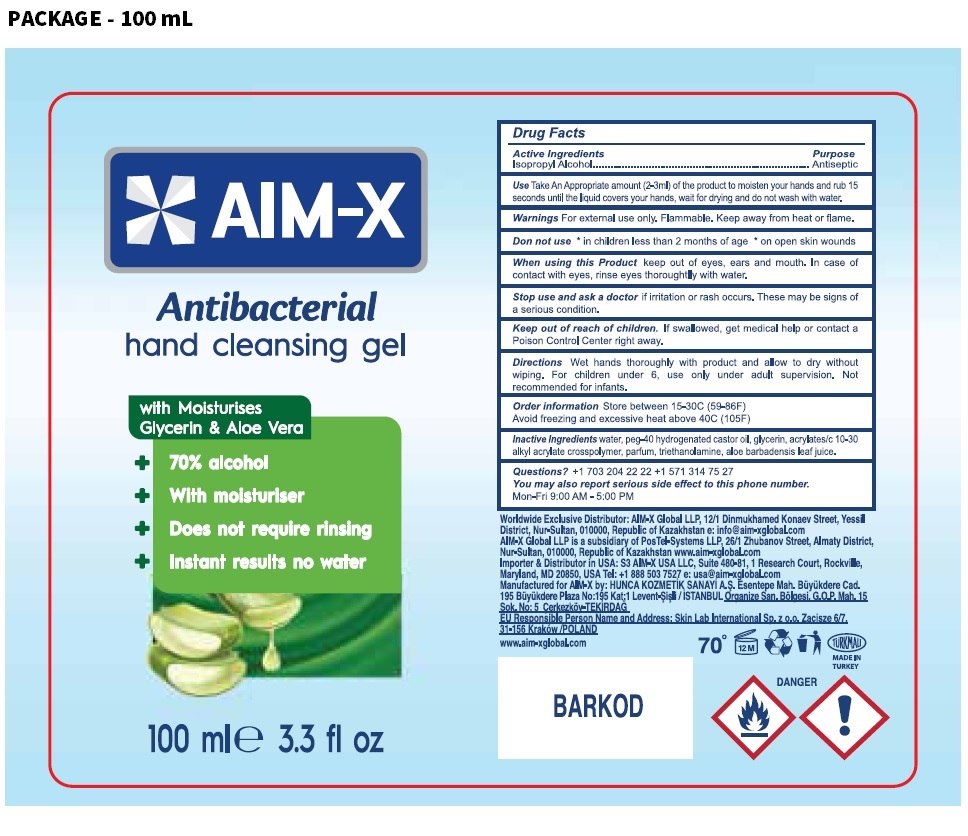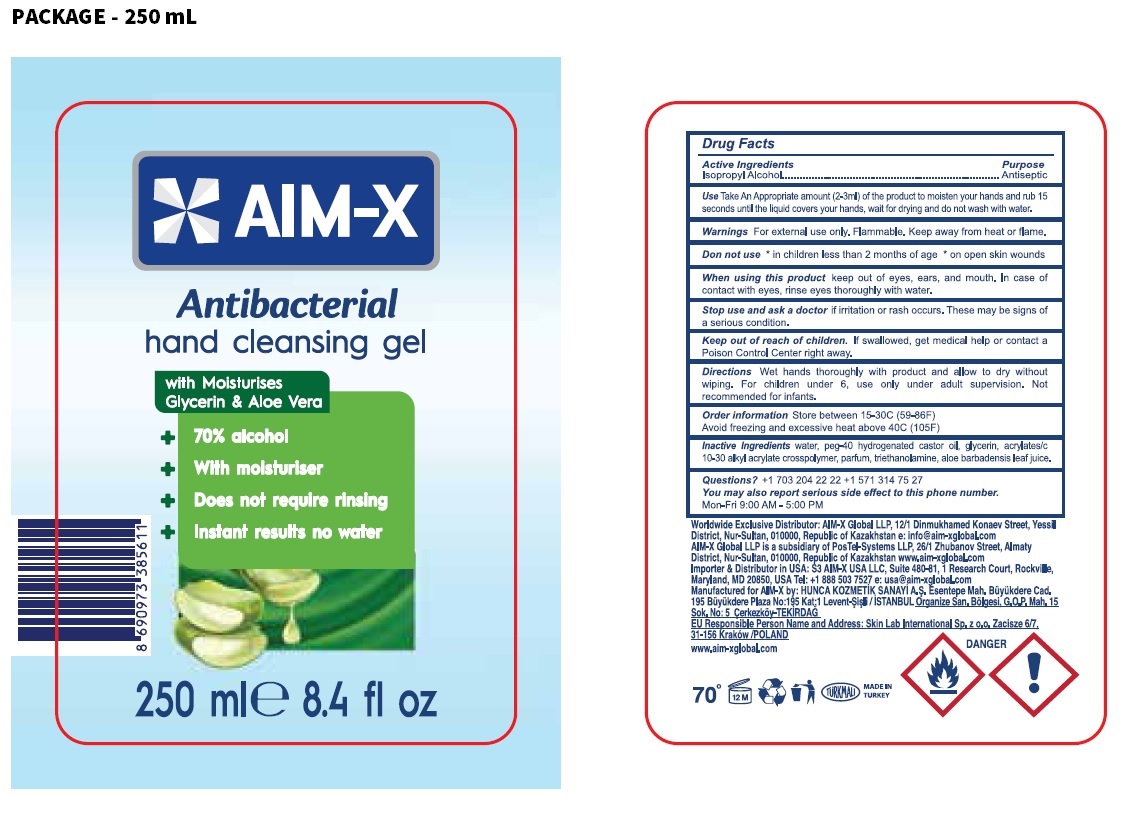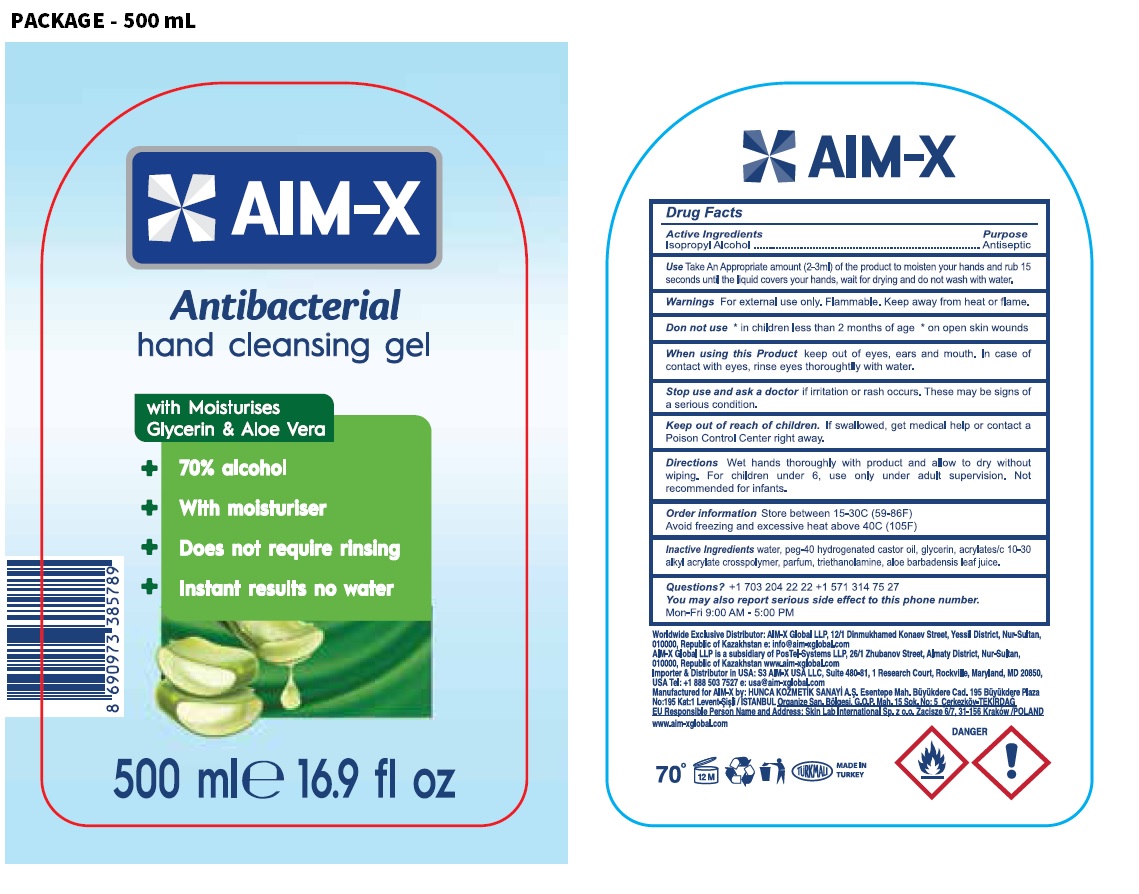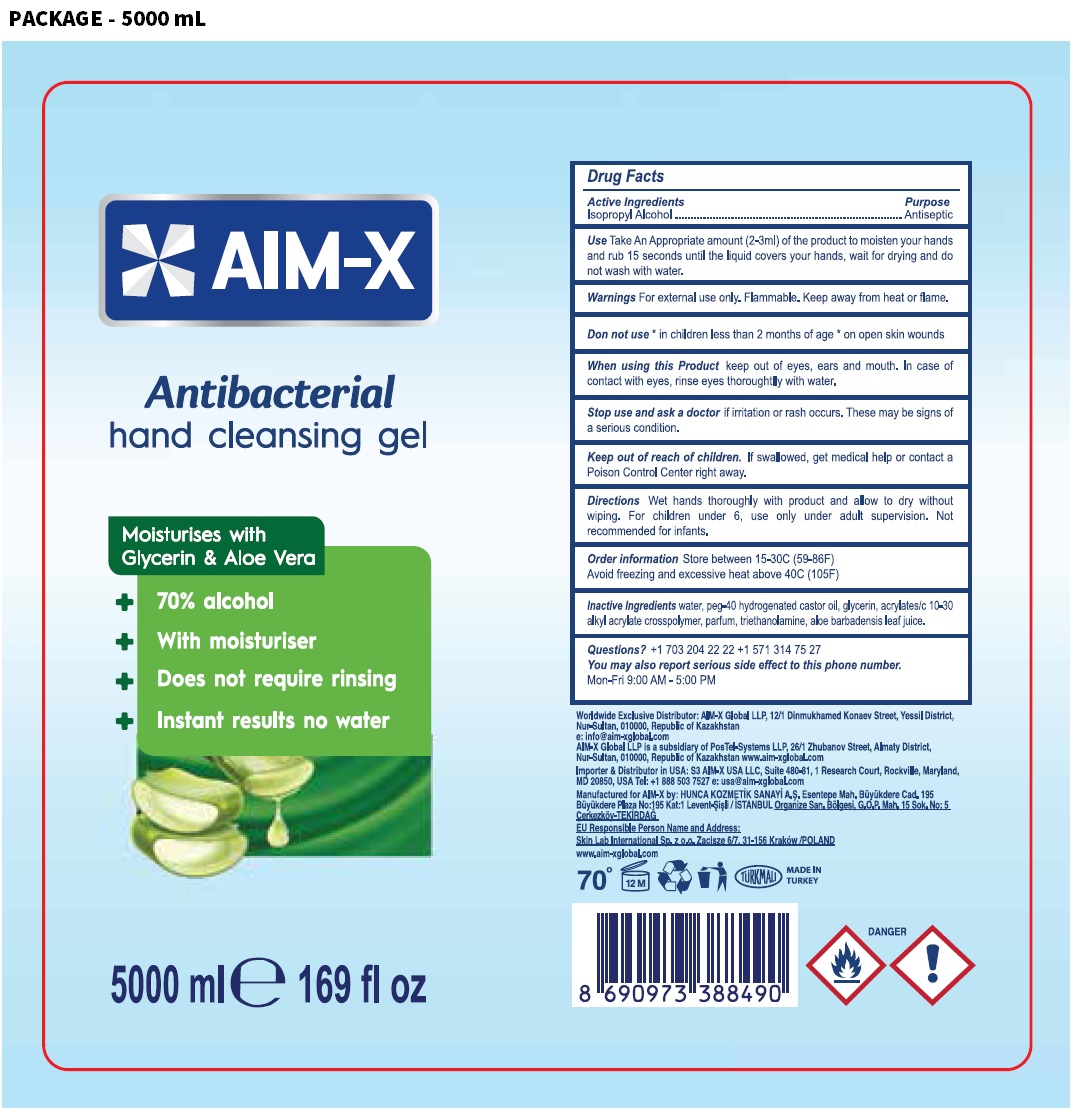 DRUG LABEL: AIM-X antibacterial hand cleansing gel
NDC: 81410-102 | Form: GEL
Manufacturer: AIM-X GLOBAL, TOO.
Category: otc | Type: HUMAN OTC DRUG LABEL
Date: 20210115

ACTIVE INGREDIENTS: ISOPROPYL ALCOHOL 70 mL/100 mL
INACTIVE INGREDIENTS: WATER; POLYOXYL 40 HYDROGENATED CASTOR OIL; GLYCERIN; CARBOMER INTERPOLYMER TYPE A (ALLYL SUCROSE CROSSLINKED); TROLAMINE; ALOE VERA LEAF

AIM-X Antibacterial hand cleansing gel

Active Ingredients

Isopropyl Alcohol

Purpose

Antiseptic

Use

Take An Appropriate amount (2-3ml) of the product to moisten your hands and rub 15 seconds until the liquid covers your hands, wait for drying and do not wash with water.

Warnings

For external use only. Flammable. Keep away from heat or flame.

Do not use * in children less than 2 months of age * on open skin wounds

When using this Product keep out of eyes, ears and mouth. In case of contact with eyes, rinse eyes thoroughly with water.

Stop use and ask a doctor if irritation or rash occurs. These may be signs of a serious condition.

Keep out of reach of children. If swallowed, get medical help or contact a Poison Control Center right away.

Directions

Wet hands thoroughly with product and allow to dry without wiping. For children under 6, use only under adult supervision. Not recommended for infants.

Other information

Store between 15-30C (59-86F)

Avoid freezing and excessive heat above 40C (105F)

Inactive Ingredients

water, peg-40 hydrogenated castor oil, glycerin, acrylates/c 10-30 alkyl acrylate crosspolymer, parfum, triethanolamine, aloe barbadensis leaf juice.

Questions?

+1 703 204 22 22 +1 571 314 75 27

You may also report serious side effect to this phone number. Mon-Fri 9:00 AM - 5:00 PM

with Moisturises

Glycerin & Aloe Vera

+ 70% alcohol

+ with moisturiser

+ Does not require rinsing

+ Instant results no water

Worldwide Exclusive Distributor: AIM-X Global LLP, 12/1 Dinmukhamed Konaev Street, Yessil District, Nur-Sultan, 010000, Republic of Kazakhstan

e: info@aim-xglobal.com

AIM-X Global LLP is a subsidiary of PosTel-Systems LLP, 26/1 Zhubanov Street, Almaty District, Nur-Sultan, 010000, Republic of Kazakhstan www.aim-xglobal.com

Importer & Distributor in USA: S3 AIM-X USA LLC, Suite 480-81, 1 Research Court, Rockville, Maryland, MD 20850,

USA Tel: +1 888 503 7527 e: usa@aim-xglobal.com

Manufactured for AIM-X by: HUNCA KOZMETIK SANAYI A.S. Esentepe Mah. Büyükdere Cad. 195 Büyükdere Plaza No: 195 Kat:1

Levent-Sisli/ ISTANBUL Organize San. Bölgesi, G.O.P. Mah. 15 Sok. No: 5 Cerkezköy-TEKIRDAG

EU Responsible Person Name and Address: Skin Lab International Sp.z o.o. Zacisze 6/7, 31-156 Kraków /POLAND

www.aim-xglobal.com

TÜRKMALI

MADE IN TURKEY